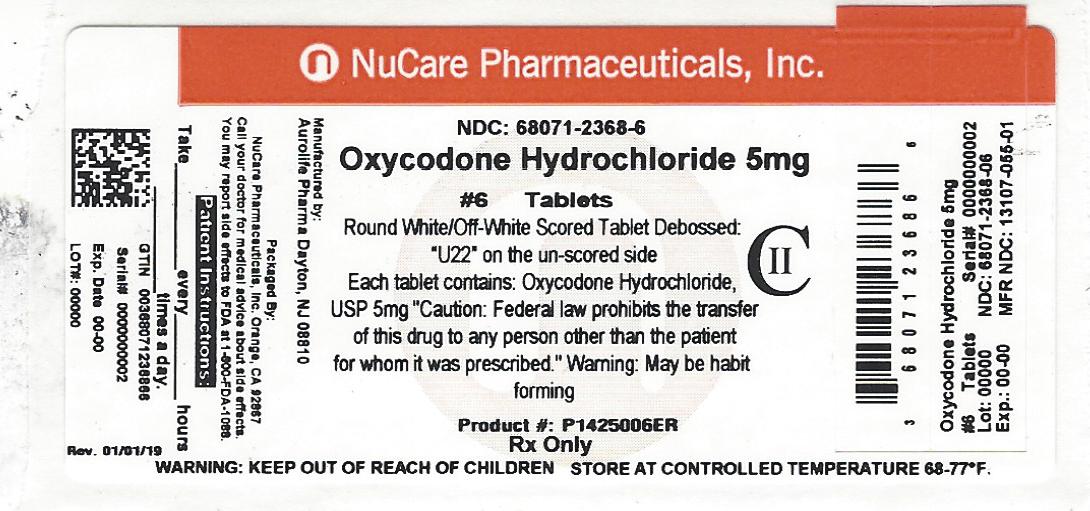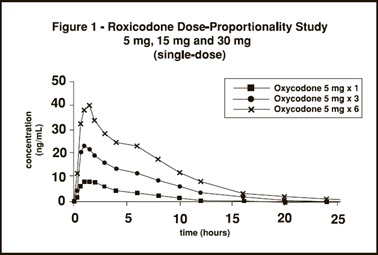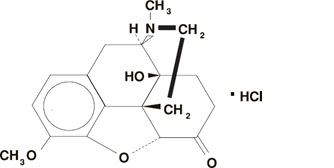 DRUG LABEL: Oxycodone Hydrochloride
NDC: 68071-2368 | Form: TABLET
Manufacturer: NuCare Pharmaceuticals,Inc.
Category: prescription | Type: HUMAN PRESCRIPTION DRUG LABEL
Date: 20260220
DEA Schedule: CII

ACTIVE INGREDIENTS: OXYCODONE HYDROCHLORIDE 5 mg/1 1
INACTIVE INGREDIENTS: CELLULOSE, MICROCRYSTALLINE; STEARIC ACID; LACTOSE MONOHYDRATE; ANHYDROUS LACTOSE; STARCH, CORN

HIGHLIGHTS OF PRESCRIBING INFORMATION
These highlights do not include all the information needed to use Oxycodone Hydrochloride Tablets safely and effectively. See full prescribing information for Oxycodone Hydrochloride Tablets.
OXYCODONE HYDROCHLORIDE TABLETS, for oral use, CII Initial U.S. Approval: 1950

RECENT MAJOR CHANGES

Boxed Warning 09/2018
Warnings and Precautions (5.2) 09/2018

BOXED WARNING

WARNING: ADDICTION, ABUSE, AND MISUSE; RISK EVALUATION AND MITIGATION STRATEGY (REMS); LIFE THREATENING RESPIRATORY DEPRESSION; ACCIDENTAL INGESTION; NEONATAL OPIOID WITHDRAWAL SYNDROME; CYTOCHROME P450 3A4 INTERACTION; and RISKS FROM CONCOMITANT USE WITH BENZODIAZEPINES OR OTHER CNS DEPRESSANTS
See full prescribing information for complete boxed warning.

- Oxycodone Hydrochloride Tablets exposes users to risks of addiction, abuse, and misuse, which can lead to overdose and death. Assess patient’s risk before prescribing and monitor regularly for these behaviors and conditions. (5.1)
- To ensure that the benefits of opioid analgesics outweigh the risks of addiction, abuse, and misuse, the Food and Drug Administration (FDA) has required a Risk Evaluation and Mitigation Strategy (REMS) for these products. (5.2)
- Serious, life-threatening, or fatal respiratory depression may occur. Monitor closely, especially upon initiation or following a dose increase. (5.3)
- Accidental ingestion of Oxycodone Hydrochloride Tablets , especially by children, can result in a fatal overdose of oxycodone. (5.3)
- Prolonged use of Oxycodone Hydrochloride Tablets during pregnancy can result in neonatal opioid withdrawal syndrome, which may be life- threatening if not recognized and treated. If prolonged opioid use is required in a pregnant woman, advise the patient of the risk of neonatal opioid withdrawal syndrome and ensure that appropriate treatment will be available. (5.4)
- Concomitant use with CYP3A4 inhibitors (or discontinuation of CYP3A4 inducers) can result in a fatal overdose of oxycodone from Oxycodone Hydrochloride Tablets. (5.5, 7, 12.3)
- Concomitant use of opioids with benzodiazepines or other central nervous system (CNS) depressants, including alcohol, may result in profound sedation, respiratory depression, coma, and death. Reserve concomitant prescribing for use in patients for whom alternative treatment options are inadequate; limit dosages and durations to the minimum required; and follow patients for signs and symptoms of respiratory depression and sedation. (5.6, 7)

1 INDICATIONS & USAGE

Oxycodone Hydrochloride Tablets is an opioid agonist indicated for the management of pain severe enough to require an opioid analgesic and for which alternative treatments are inadequate. (1)

Limitations of Use (1)
Because of the risks of addiction, abuse, and misuse with opioids, even at recommended doses, reserve Oxycodone Hydrochloride Tablets for use in patients for whom alternative treatment options (e.g., non-opioid analgesics or non-opioid combination products):

- Have not been tolerated, or are not expected to be tolerated,
- Have not provided adequate analgesia or are not expected to provide adequate analgesia.

2 DOSAGE & ADMINISTRATION

- Use the lowest effective dosage for the shortest duration consistent with individual patient treatment goals. (2.1)
- Individualize dosing based on severity of pain, patient response, prior analgesic experience, and risk factors for addiction, abuse and misuse. (2.1)
- Initiate dosing with a range of 5 to 15 mg every 4 to 6 hours as needed for pain. (2.2)
- For control of chronic pain, administer Oxycodone Hydrochloride Tablets on a regularly scheduled basis, at the lowest dosage level to achieve adequate analgesia. (2.2)
- Individually titrate Oxycodone Hydrochloride Tablets to a dose that provides adequate analgesia and minimizes adverse reactions. (2.3)
- Do not stop Oxycodone Hydrochloride Tablets abruptly in a physically dependent patient. (2.4)

3 DOSAGE FORMS & STRENGTHS

Immediate-release tablets: 5 mg, 15 mg, 30 mg (3)

4 CONTRAINDICATIONS

- Significant respiratory depression (4)
- Acute or severe bronchial asthma in an unmonitored setting or in absence of resuscitative equipment (4)
- Known or suspected gastrointestinal obstruction, including paralytic ileus (4)
- Hypersensitivity to oxycodone (4)

5 WARNINGS AND PRECAUTIONS

- Life-Threatening Respiratory Depression in Patients with Chronic Pulmonary Disease or in Elderly, Cachectic, or Debilitated Patients: Monitor closely, particularly during initiation and titration. (5.7)
- Adrenal Insufficiency: If diagnosed, treat with physiologic replacement of corticosteroids, and wean patient off of the opioid. (5.8)
- Severe Hypotension: Monitor during dosage initiation and titration. Avoid use of Oxycodone Hydrochloride Tablets in patients with circulatory shock. (5.9)
- Risks of Use in Patients with Increased Intracranial Pressure, Brain Tumors, Head Injury, or Impaired Consciousness: Monitor for sedation and respiratory depression. Avoid use of Oxycodone Hydrochloride Tablets in patients with impaired consciousness or coma. (5.10)

6 ADVERSE REACTIONS

Most common adverse reactions (≥3%) were nausea, constipation, vomiting, headache, pruritus, insomnia, dizziness, asthenia, and somnolence. (6.1)

To report SUSPECTED ADVERSE REACTIONS, contact Mallinckrodt at 1-800-778-7898 or FDA at 1-800-FDA-1088 or www.fda.gov/medwatch.

7 DRUG INTERACTIONS

- Serotonergic Drugs: Concomitant use may result in serotonin syndrome. Discontinue Oxycodone Hydrochloride Tablets if serotonin syndrome is suspected. (7)
- Mixed Agonist/Antagonist and Partial Agonist Opioid Analgesics: Avoid use with Oxycodone Hydrochloride Tablets because they may reduce analgesic effect of Oxycodone Hydrochloride Tablets or precipitate withdrawal symptoms. (7)
- Monoamine Oxidase Inhibitors (MAOIs): Can potentiate the effects of morphine. Avoid concomitant use in patients receiving MAOIs or within 14 days of stopping treatment with an MAOI. (7)

8 USE IN SPECIFIC POPULATIONS

- Pregnancy: May cause fetal harm. (8.1)

FULL PRESCRIBING INFORMATION

BOXED WARNING

WARNING: ADDICTION, ABUSE, AND MISUSE; RISK EVALUATION AND MITIGATION STRATEGY (REMS); LIFE-THREATENING RESPIRATORY DEPRESSION; ACCIDENTAL INGESTION; NEONATAL OPIOID WITHDRAWAL SYNDROME; CYTOCHROME P450 3A4 INTERACTION; and RISKS FROM CONCOMITANT USE WITH BENZODIAZEPINES OR OTHER CNS DEPRESSANTS

Addiction, Abuse, and Misuse
Oxycodone Hydrochloride Tablets exposes patients and other users to the risks of opioid addiction, abuse, and misuse, which can lead to overdose and death. Assess each patient’s risk prior to prescribing Oxycodone Hydrochloride Tablets, and monitor all patients regularly for the development of these behaviors and conditions [see Warnings and Precautions (5.1)].
Opioid Analgesic Risk Evaluation and Mitigation Strategy (REMS)
To ensure that the benefits of opioid analgesics outweigh the risks of addiction, abuse, and misuse, the Food and Drug Administration (FDA) has required a REMS for these products [see Warnings and Precautions (5.2)]. Under the requirements of the REMS, drug companies with approved opioid analgesic products must make REMS-compliant education programs available to healthcare providers. Healthcare providers are strongly encouraged to

- complete a REMS-compliant education program,
- counsel patients and/or their caregivers, with every prescription, on safe use, serious risks, storage, and disposal of these products,
- emphasize to patients and their caregivers the importance of reading the Medication Guide every time it is provided by their pharmacist, and
- Consider other tools to improve patient, household, and community safety.

Life-Threatening Respiratory Depression
Serious, life-threatening, or fatal respiratory depression may occur with use of Oxycodone Hydrochloride Tablets. Monitor for respiratory depression, especially during initiation of Oxycodone Hydrochloride Tablets or following a dose increase [see Warnings and Precautions (5.3)].
Accidental Ingestion
Accidental ingestion of even one dose of Oxycodone Hydrochloride Tablets, especially by children, can result in a fatal overdose of oxycodone [see Warnings and Precautions (5.3)].
Neonatal Opioid Withdrawal Syndrome
Prolonged use of Oxycodone Hydrochloride Tablets during pregnancy can result in neonatal opioid withdrawal syndrome, which may be life-threatening if not recognized and treated, and requires management according to protocols developed by neonatology experts. If opioid use is required for a prolonged period in a pregnant woman, advise the patient of the risk of neonatal opioid withdrawal syndrome and ensure that appropriate treatment will be available [see Warnings and Precautions (5.4)].

Cytochrome P450 3A4 Interaction

- The concomitant use of Oxycodone Hydrochloride Tablets with all cytochrome P450 3A4 inhibitors may result in an increase in oxycodone plasma concentrations, which could increase or prolong adverse reactions and may cause potentially fatal respiratory depression. In addition, discontinuation of a concomitantly used cytochrome P450 3A4 inducer may result in an increase in oxycodone plasma concentration. Monitor patients receiving Oxycodone Hydrochloride Tablets and any CYP3A4 inhibitor or inducer [see Warnings and Precautions (5.5), Drug Interactions (7), Clinical Pharmacology (12.3)].

Risks from Concomitant Use with Benzodiazepines or Other CNS Depressants
Concomitant use of opioids with benzodiazepines or other central nervous system (CNS) depressants, including alcohol, may result in profound sedation, respiratory depression, coma, and death [see Warnings and Precautions (5.6), Drug Interactions (7)].

- Reserve concomitant prescribing of ROXICODONE and benzodiazepines or other CNS depressants for use in patients for whom alternative treatment options are inadequate.
- Limit dosages and durations to the minimum required.
- Follow patients for signs and symptoms of respiratory depression and sedation.

1 INDICATIONS & USAGE

Oxycodone Hydrochloride Tablets is indicated for the management of pain severe enough to require an opioid analgesic and for which alternative treatments are inadequate.

Limitations of Use
Because of the risks of addiction, abuse, and misuse with opioids, even at recommended doses [see Warnings and Precautions (5.1)],reserve Oxycodone Hydrochloride Tablets for use in patients for whom alternative treatment options (e.g., non-opioid analgesics or opioid combination products):

- Have not been tolerated or are not expected to be tolerated,
- Have not provided adequate analgesia or are not expected to provide adequate analgesia.

2 DOSAGE & ADMINISTRATION

2.1 Important Dosage and Administration Instructions

Use the lowest effective dosage for the shortest duration consistent with individual patient treatment goals [see Warnings and Precautions (5)].

Initiate the dosing regimen for each patient individually, taking into account the patient's severity of pain, patient response, prior analgesic treatment experience, and risk factors for addiction, abuse, and misuse [see Warnings and Precautions (5.1)].

Monitor patients closely for respiratory depression, especially within the first 24 to 72 hours of initiating therapy and following dosage increases with Oxycodone Hydrochloride Tablets and adjust the dosage accordingly [see Warnings and Precautions (5.3)].

2.2 Initial Dose

Use of Oxycodone Hydrochloride Tablets as the First Opioid Analgesic
Initiate treatment with Oxycodone Hydrochloride Tablets in a dosing range of 5 to 15 mg every 4 to 6 hours as needed for pain. Titrate the dose based upon the individual patient’s response to their initial dose of Oxycodone Hydrochloride Tablets. Patients with chronic pain should have their dosage given on an around-the-clock basis to prevent the reoccurrence of pain rather than treating the pain after it has occurred. This dose can then be adjusted to an acceptable level of analgesia taking into account side effects experienced by the patient.

For control of severe chronic pain, Oxycodone Hydrochloride Tablets should be administered on a regularly scheduled basis, every 4 to 6 hours, at the lowest dosage level that will achieve adequate analgesia.

Although it is not possible to list every condition that is important to the selection of the initial dose of Oxycodone Hydrochloride Tablets , attention should be given to: 1) the daily dose, potency, and characteristics of a purefull agonist or mixed agonist/antagonist the patient has been taking previously, 2) the reliability of the relative potency estimate to calculate the dose of oxycodone needed, 3) the degree of opioid tolerance, 4) the general condition and medical status of the patient, and 5) the balance between pain control and adverse experiences.

Conversion from Other Opioids to Oxycodone Hydrochloride Tablets
There is inter-patient variability in the potency of opioid drugs and opioid formulations. Therefore, a conservative approach is advised when determining the total daily dosage of Oxycodone Hydrochloride Tablets. It is safer to underestimate a patient’s 24-hour Oxycodone Hydrochloride Tablets dosage than to overestimate the 24-hour Oxycodone Hydrochloride Tablets dosage and manage an adverse reaction due to overdose. If a patient has been receiving opioid-containing medications prior to taking Oxycodone Hydrochloride Tablets, the potency of the prior opioid relative to oxycodone should be factored into the selection of the total daily dose (TDD) of oxycodone.

In converting patients from other opioids to Oxycodone Hydrochloride Tablets close observation and adjustment of dosage based upon the patient’s response to Oxycodone Hydrochloride Tablets is imperative. Administration of supplemental analgesia for breakthrough or incident pain and titration of the total daily dose of Oxycodone Hydrochloride Tablets may be necessary, especially in patients who have disease states that are changing rapidly.

Conversion from Fixed-Ratio Opioid/Acetaminophen, Opioid/Aspirin, or Opioid/Nonsteroidal Combination Drugs
When converting patients from fixed ratio opioid/non-opioid drug regimens a decision should be made whether or not to continue the non-opioid analgesic. If a decision is made to discontinue the use of non-opioid analgesic, it may be necessary to titrate the dose of Oxycodone Hydrochloride Tablets in response to the level of analgesia and adverse effects afforded by the dosing regimen. If the non-opioid regimen is continued as a separate single entity agent, the starting dose Oxycodone Hydrochloride Tablets should be based upon the most recent dose of opioid as a baseline for further titration of oxycodone. Incremental increases should be gauged according to side effects to an acceptable level of analgesia.

Conversion from Oxycodone Hydrochloride Tablets to Extended-Release Oxycodone
The relative bioavailability of Oxycodone Hydrochloride Tablets compared to extended-release oxycodone is unknown, so conversion to extended-release tablets must be accompanied by close observation for signs of excessive sedation and respiratory depression.

2.3 Titration and Maintenance of Therapy

Individually titrate Oxycodone Hydrochloride Tablets to a dose that provides adequate analgesia and minimizes adverse reactions. Continually reevaluate patients receiving Oxycodone Hydrochloride Tablets to assess the maintenance of pain control and the relative incidence of adverse reactions, as well as monitoring for the development of addiction, abuse, or misuse [see Warnings and Precautions (5.1)]. Frequent communication is important among the prescriber, other members of the healthcare team, the patient, and the caregiver/family during periods of changing analgesic requirements, including initial titration.

If the level of pain increases after dosage stabilization, attempt to identify the source of increased pain before increasing the Oxycodone Hydrochloride Tablets dosage. If unacceptable opioid-related adverse reactions are observed, consider reducing the dosage. Adjust the dosage to obtain an appropriate balance between management of pain and opioid-related adverse reactions.

2.4 Discontinuation of OXYCODONE HYDROCHLORIDE TABLETS

When a patient who has been taking Oxycodone Hydrochloride Tablets regularly and may be physically dependent no longer requires therapy with Oxycodone Hydrochloride Tablets , taper the dose gradually, by 25% to 50% every 2 to 4 days, while monitoring carefully for signs and symptoms of withdrawal. If the patient develops these signs or symptoms, raise the dose to the previous level and taper more slowly, either by increasing the interval between decreases, decreasing the amount of change in dose, or both. Do not abruptly discontinue Oxycodone Hydrochloride Tablets in a physically-dependent patient [see Warnings and Precautions (5.1), Drug Abuse and Dependence (9.3)].

3 DOSAGE FORMS & STRENGTHS

Oxycodone Hydrochloride Tablets, USP:

5 mg white to off white, round tablets, debossed with “U22” on one side and break line on the other side.
15 mg light green to green, round tablets, debossed with “U23” on one side and break line on the other side.
30 mg light blue to blue, round tablets, debossed with “U24” on one side and break line on the other side.

4 CONTRAINDICATIONS

Oxycodone Hydrochloride Tablets is contraindicated in patients with:

- Significant respiratory depression [see Warnings and Precautions (5.3)].
- Acute or severe bronchial asthma in an unmonitored setting or in the absence of resuscitative equipment or hypercarbia [see Warnings and Precautions (5.7)].
- Known or suspected gastrointestinal obstruction, including paralytic ileus [see Warnings and Precautions (5.11)].
- Known hypersensitivity (e.g., anaphylaxis) to oxycodone [see Adverse Reactions (6.2)].

5 WARNINGS AND PRECAUTIONS

5.1 Addiction, Abuse, and Misuse

Oxycodone Hydrochloride Tablets contains oxycodone, a Schedule II controlled substance. As an opioid, Oxycodone Hydrochloride Tablets exposes users to the risks of addiction, abuse, and misuse [see Drug Abuse and Dependence (9)].

Although the risk of addiction in any individual is unknown, it can occur in patients appropriately prescribed Oxycodone Hydrochloride Tablets. Addiction can occur at recommended dosages and if the drug is misused or abused.

Assess each patient’s risk for opioid addiction, abuse, or misuse prior to prescribing Oxycodone Hydrochloride Tablets, and monitor all patients receiving Oxycodone Hydrochloride Tablets for the development of these behaviors and conditions. Risks are increased in patients with a personal or family history of substance abuse (including drug or alcohol abuse or addiction) or mental illness (e.g., major depression). The potential for these risks should not, however, prevent the proper management of pain in any given patient. Patients at increased risk may be prescribed opioids such as Oxycodone Hydrochloride Tablets, but use in such patients necessitates intensive counseling about the risks and proper use of Oxycodone Hydrochloride Tablets along with intensive monitoring for signs of addiction, abuse, and misuse.

Opioids are sought by drug abusers and people with addiction disorders and are subject to criminal diversion. Consider these risks when prescribing or dispensing Oxycodone Hydrochloride Tablets. Strategies to reduce these risks include prescribing the drug in the smallest appropriate quantity and advising the patient on the proper disposal of unused drugs [see Patient Counseling Information (17)]. Contact local state professional licensing board or state controlled substances authority for information on how to prevent and detect abuse or diversion of this product.

5.2 Opioid Analgesic Risk Evaluation and Mitigation Strategy (REMS)

To ensure that the benefits of opioid analgesics outweigh the risks of addiction, abuse, and misuse, the Food and Drug Administration (FDA) has required a Risk Evaluation and Mitigation Strategy (REMS) for these products. Under the requirements of the REMS, drug companies with approved opioid analgesic products must make REMS-compliant education programs available to healthcare providers. Healthcare providers are strongly encouraged to do all of the following:

- Complete a REMS-compliant education program offered by an accredited provider of continuing education (CE) or another education program that includes all the elements of the FDA Education Blueprint for Health Care Providers Involved in the Management or Support of Patients with Pain.
- Discuss the safe use, serious risks, and proper storage and disposal of opioid analgesics with patients and/or their caregivers every time these medicines are prescribed. The Patient Counseling Guide (PCG) can be obtained at this link: www.fda.gov/OpioidAnalgesicREMSPCG.
- Emphasize to patients and their caregivers the importance of reading the Medication Guide that they will receive from their pharmacist every time an opioid analgesic is dispensed to them.
- Consider using other tools to improve patient, household, and community safety, such as patient-prescriber agreements that reinforce patient-prescriber responsibilities.

To obtain further information on the opioid analgesic REMS and for a list of accredited REMS CME/CE, call 1-800-503-0784, or log on to www.opioidanalgesicrems.com. The FDA Blueprint can be found at www.fda.gov/OpioidAnalgesicREMSBlueprint.

5.3 Life-Threatening Respiratory Depression

Serious, life-threatening, or fatal respiratory depression has been reported with the use of opioids, even when used as recommended. Respiratory depression, if not immediately recognized and treated, may lead to respiratory arrest and death. Management of respiratory depression may include close observation, supportive measures, and use of opioid antagonists, depending on the patient’s clinical status [see Overdosage (10)]. Carbon dioxide (CO2) retention from opioid-induced respiratory depression can exacerbate the sedating effects of opioids.

While serious, life-threatening, or fatal respiratory depression can occur at any time during the use of Oxycodone Hydrochloride Tablets, the risk is greatest during the initiation of therapy or following a dosage increase. Monitor patients closely for respiratory depression, especially within the first 24 to 72 hours of initiating therapy with and following dosage increases of Oxycodone Hydrochloride Tablets
To reduce the risk of respiratory depression, proper dosing and titration of Oxycodone Hydrochloride Tablets are essential [see Dosage and Administration (2)]. Overestimating the Oxycodone Hydrochloride Tablets dosage when converting patients from another opioid product can result in fatal overdose with the first dose.

Accidental ingestion of even one dose of Oxycodone Hydrochloride Tablets, especially by children, can result in respiratory depression and death due to an overdose of oxycodone.

5.4 Neonatal Opioid Withdrawal Syndrome

Prolonged use of Oxycodone Hydrochloride Tablets during pregnancy can result in withdrawal in the neonate. Neonatal opioid withdrawal syndrome, unlike opioid withdrawal syndrome in adults, may be life-threatening if not recognized and treated, and requires management according to protocols developed by neonatology experts. Observe newborns for signs of neonatal opioid withdrawal syndrome and manage accordingly. Advise pregnant women using opioids for a prolonged period of the risk of neonatal opioid withdrawal syndrome and ensure that appropriate treatment will be available [see Use in Specific Populations (8.1), Patient Counseling Information (17)].

5.5 Risks of Concomitant Use or Discontinuation of Cytochrome P450 3A4 Inhibitors and Inducers

Concomitant use of Oxycodone Hydrochloride Tablets with a CYP3A4 inhibitor, such as macrolide antibiotics (e.g., erythromycin), azole-antifungal agents (e.g., ketoconazole), and protease inhibitors (e.g., ritonavir), may increase plasma concentrations of oxycodone and prolong opioid adverse reactions, which may cause potentially fatal respiratory depression [see Warnings and Precautions (5.3)], particularly when an inhibitor is added after a stable dose of Oxycodone Hydrochloride Tablets is achieved. Similarly, discontinuation of a CYP3A4 inducer, such as rifampin, carbamazepine, and phenytoin, in Oxycodone Hydrochloride Tablets treated patients may increase oxycodone plasma concentrations and prolong opioid adverse reactions. When using Oxycodone Hydrochloride Tablets with CYP3A4 inhibitors or discontinuing CYP3A4 inducers in Oxycodone Hydrochloride Tablets- treated patients, monitor patients closely at frequent intervals and consider dosage reduction of Oxycodone Hydrochloride Tablets until stable drugs effects are achieved [see Drug Interactions (7)].

Concomitant use of Oxycodone Hydrochloride Tablets with CYP3A4 inducers or discontinuation of an CYP3A4 inhibitor could decrease oxycodone plasma concentrations, decrease opioid efficacy or, possibly, lead to a withdrawal syndrome in a patient who had developed physical dependence to oxycodone. When using Oxycodone Hydrochloride Tablets with CYP3A4 inducers or discontinuing CYP3A4 inhibitors, monitor patients closely at frequent intervals and consider increasing the opioid dosage if needed to maintain adequate analgesia or if symptoms of opioid withdrawal occur [see Drug Interactions (7)].

5.6 Risks from Concomitant Use with Benzodiazepines or Other CNS Depressants

Profound sedation, respiratory depression, coma, and death may result from the concomitant use of Oxycodone Hydrochloride Tablets with benzodiazepines or other CNS depressants (e.g., non-benzodiazepine sedatives/hypnotics, anxiolytics, tranquilizers, muscle relaxants, general anesthetics, antipsychotics, other opioids, alcohol). Because of these risks, reserve concomitant prescribing of these drugs for use in patients for whom alternative treatment options are inadequate.

Observational studies have demonstrated that concomitant use of opioid analgesics and benzodiazepines increases the risk of drug-related mortality compared to use of opioid analgesics alone. Because of similar pharmacological properties, it is reasonable to expect similar risk with the concomitant use of other CNS depressant drugs with opioid analgesics [see Drug Interactions (7)].

If the decision is made to prescribe a benzodiazepine or other CNS depressant concomitantly with an opioid analgesic, prescribe the lowest effective dosages and minimum durations of concomitant use. In patients already receiving an opioid analgesic, prescribe a lower initial dose of the benzodiazepine or other CNS depressant than indicated in the absence of an opioid, and titrate based on clinical response. If an opioid analgesic is initiated in a patient already taking a benzodiazepine or other CNS depressant, prescribe a lower initial dose of the opioid analgesic, and titrate based on clinical response. Follow patients closely for signs and symptoms of respiratory depression and sedation.
Advise both patients and caregivers about the risks of respiratory depression and sedation when Oxycodone Hydrochloride Tablets is used with benzodiazepines or other CNS depressants (including alcohol and illicit drugs). Advise patients not to drive or operate dangerous machinery until the effects of concomitant use of the benzodiazepine or other CNS depressant have been determined. Screen patients for risk of substance use disorders, including opioid abuse and misuse, and warn them of the risk for overdose and death associated with the use of additional CNS depressants including alcohol and illicit drugs [see Drug Interactions (7), Patient Counseling Information (17)].

5.7 Life-Threatening Respiratory Depression in Patients with Chronic Pulmonary Disease or in Elderly, Cachectic, or Debilitated Patients

The use of Oxycodone Hydrochloride Tablets in patients with acute or severe bronchial asthma in an unmonitored setting or in the absence of resuscitative equipment is contraindicated.

Patients with Chronic Pulmonary Disease: Oxycodone Hydrochloride Tablets-treated patients with significant chronic obstructive pulmonary disease or cor pulmonale, and those with a substantially decreased respiratory reserve, hypoxia, hypercapnia, or pre-existing respiratory depression are at increased risk of decreased respiratory drive including apnea, even at recommended dosages of Oxycodone Hydrochloride Tablets [see Warnings and Precautions (5.3)].

Elderly, Cachectic, or Debilitated Patients: Life-threatening respiratory depression is more likely to occur in elderly, cachectic, or debilitated patients because they may have altered pharmacokinetics or altered clearance compared to younger, healthier patients [see Warnings and Precautions (5.3)].

Monitor patients closely, particularly when initiating and titrating Oxycodone Hydrochloride Tablets and when Oxycodone Hydrochloride Tablets is given concomitantly with other drugs that depress respiration [see Warnings and Precautions (5.3)]. Alternatively, consider the use of non-opioid analgesics in these patients.

5.8 Adrenal Insufficiency

Cases of adrenal insufficiency have been reported with opioid use, more often following greater than one month of use. Presentation of adrenal insufficiency may include non-specific symptoms and signs including nausea, vomiting, anorexia, fatigue, weakness, dizziness, and low blood pressure. If adrenal insufficiency is suspected, confirm the diagnosis with diagnostic testing as soon as possible. If adrenal insufficiency is diagnosed, treat with physiologic replacement doses of corticosteroids. Wean the patient off of the opioid to allow adrenal function to recover and continue corticosteroid treatment until adrenal function recovers. Other opioids may be tried as some cases reported use of a different opioid without recurrence of adrenal insufficiency. The information available does not identify any particular opioids as being more likely to be associated with adrenal insufficiency.

5.9 Severe Hypotension

Oxycodone Hydrochloride Tablets may cause severe hypotension including orthostatic hypotension and syncope in ambulatory patients. There is increased risk in patients whose ability to maintain blood pressure has already been compromised by a reduced blood volume or concurrent administration of certain CNS depressant drugs (e.g., phenothiazines or general anesthetics) [see Drug Interactions (7)]. Monitor these patients for signs of hypotension after initiating or titrating the dosage of Oxycodone Hydrochloride Tablets. In patients with circulatory shock, use of Oxycodone Hydrochloride Tablets may cause vasodilation that can further reduce cardiac output and blood pressure. Avoid use of Oxycodone Hydrochloride Tablets in patients with circulatory shock.
Risks of Use in Patients with Increased Intracranial Pressure, Brain Tumors, Head Injury, or Impaired Consciousness
In patients who may be susceptible to the intracranial effects of CO2 retention (e.g., those with evidence of increased intracranial pressure or brain tumors), Oxycodone Hydrochloride Tablets may reduce the respiratory drive, and the resultant CO2 retention can further increase intracranial pressure. Monitor such patients for signs of sedation and respiratory depression, particularly when initiating therapy with Oxycodone Hydrochloride Tablets.

Opioids may obscure the clinical course in a patient with a head injury. Avoid the use of Oxycodone Hydrochloride Tablets in patients with impaired consciousness or coma.

5.10 Risks of Use in Patients with Increased Intracranial Pressure, Brain Tumors, Head Injury, or Impaired Consciousness

In patients who may be susceptible to the intracranial effects of CO2 retention (e.g., those with evidence of increased intracranial pressure or brain tumors), Oxycodone Hydrochloride Tablets may reduce the respiratory drive, and the resultant CO2 retention can further increase intracranial pressure. Monitor such patients for signs of sedation and respiratory depression, particularly when initiating therapy with Oxycodone Hydrochloride Tablets.

Opioids may obscure the clinical course in a patient with a head injury. Avoid the use of Oxycodone Hydrochloride Tablets in patients with impaired consciousness or coma.

5.11 Risks of Use in Patients with Gastrointestinal Conditions

Oxycodone Hydrochloride Tablets is contraindicated in patients with gastrointestinal obstruction, including paralytic ileus.

The oxycodone in Oxycodone Hydrochloride Tablets may cause spasm of the sphincter of Oddi. Opioids may cause increases in serum amylase. Monitor patients with biliary tract disease, including acute pancreatitis, for worsening symptoms.

5.12 Increased Risk of Seizures in Patients with Seizure Disorders

The oxycodone in Oxycodone Hydrochloride Tablets may increase the frequency of seizures in patients with seizure disorders, and may increase the risk of seizures occurring in other clinical settings associated with seizures. Monitor patients with a history of seizure disorders for worsened seizure control during Oxycodone Hydrochloride Tablets therapy.

5.13 Withdrawal

Avoid the use of mixed agonist/antagonist (e.g., pentazocine, nalbuphine, and butorphanol) or partial agonist (e.g., buprenorphine) analgesics in patients who are receiving a full opioid agonist analgesic, including Oxycodone Hydrochloride Tablets. In these patients, mixed agonist/antagonist and partial agonist analgesics may reduce the analgesic effect and/or precipitate withdrawal symptoms [see Drug Interactions (7)].

When discontinuing Oxycodone Hydrochloride Tablets in a physically-dependent patient, gradually taper the dosage [see Dosage and Administration (2.4)]. Do not abruptly discontinue Oxycodone Hydrochloride Tablets in these patients [see Drug Abuse and Dependence (9.3)].

5.14 Risks of Driving and Operating Machinery

Oxycodone Hydrochloride Tablets may impair the mental or physical abilities needed to perform potentially hazardous activities such as driving a car or operating machinery. Warn patients not to drive or operate dangerous machinery unless they are tolerant to the effects of Oxycodone Hydrochloride Tablets and know how they will react to the medication [see Patient Counseling Information (17)].

6 ADVERSE REACTIONS

The following serious adverse reactions are described, or described in greater detail, in other sections:

- Addiction, Abuse, and Misuse [see Warnings and Precautions (5.1)]
- Life-Threatening Respiratory Depression [see Warnings and Precautions (5.3)]
- Neonatal Opioid Withdrawal Syndrome [see Warnings and Precautions (5.4)]
- Interactions with Benzodiazepines or Other CNS Depressants [see Warnings and Precautions (5.6)]
- Adrenal Insufficiency [see Warnings and Precautions (5.8)]
- Severe Hypotension [see Warnings and Precautions (5.9)]
- Gastrointestinal Adverse Reactions [see Warnings and Precautions (5.11)]
- Seizures [see Warnings and Precautions (5.12)]
- Withdrawal [see Warnings and Precautions (5.13)]

6.1 Clinical Trials Experience

Because clinical trials are conducted under widely varying conditions, adverse reaction rates observed in the clinical trials of a drug cannot be directly compared to rates in the clinical trials of another drug and may not reflect the rates observed in practice.

Oxycodone Hydrochloride Tablets have been evaluated in open label clinical trials in patients with cancer and nonmalignant pain. Oxycodone Hydrochloride Tablets are associated with adverse experiences similar to those seen with other opioids.

Serious adverse reactions associated with Oxycodone Hydrochloride Tablets use included: respiratory depression, respiratory arrest, circulatory depression, cardiac arrest, hypotension, and/or shock.

The common adverse reactions seen on initiation of therapy with Oxycodone Hydrochloride Tablets are dose related and are typical opioid-related adverse reactions. The most frequent of these included nausea, constipation, vomiting, headache, pruritus, insomnia, dizziness, asthenia, and somnolence. The frequency of these reactions depended on several factors, including clinical setting, the patient’s level of opioid tolerance, and host factors specific to the individual.

In all patients for whom dosing information was available (n=191) from the open-label and double- blind studies involving Oxycodone Hydrochloride Tablets , the following adverse events were recorded in Oxycodone Hydrochloride Tablets treated patients with an incidence ≥ 3%. In descending order of frequency they were: nausea, constipation, vomiting, headache, pruritus, insomnia, dizziness, asthenia, and somnolence.

Other less frequently observed adverse reactions from opioid analgesics, including Oxycodone Hydrochloride Tablets included:

Blood and lymphatic system disorders: anemia, leukopenia
Cardiac disorders: cardiac failure, palpitation, tachycardia
Gastrointestinal disorders: abdominal pain, dry mouth, diarrhea, dyspepsia, dysphagia, glossitis, nausea, vomiting.

General disorders and administration site conditions: chills, edema, edema peripheral, pain, pyrexia Immune system disorders: hypersensitivity
Infections and infestations: bronchitis, gingivitis, infection, pharyngitis, rhinitis, sepsis, sinusitis, urinary tract infection

Injury, poisoning and procedural complications: injury

Metabolism and nutrition disorders: decreased appetite, gout, hyperglycemia

Musculoskeletal and connective tissue disorders: arthralgia, arthritis, back pain, bone pain, myalgia, neck pain, pathological fracture

Nervous system disorders: hypertonia, hypoesthesia, migraine, neuralgia, tremor, vasodilation
Psychiatric disorders: agitation, anxiety, confusional state, nervousness, personality disorder
Respiratory, thoracic and mediastinal disorders: cough, dyspnea, epistaxis, laryngospasm, lung disorder

Skin and subcutaneous tissue disorders: photosensitivity reaction, rash, hyperhidrosis, urticaria
Vascular disorders: thrombophlebitis, hemorrhage, hypotension, vasodilatation

6.2 Postmarketing experience

The following adverse reactions have been identified during post approval use of oxycodone. Because these reactions are reported voluntarily from a population of uncertain size, it is not always possible to reliably estimate their frequency or establish a causal relationship to drug exposure.

General disorders and administrative site disorders: drug withdrawal syndrome neonatal [see Warnings and Precautions (5.4)]

Respiratory, thoracic and mediastinal disorders: pharyngeal edema

Serotonin syndrome: Cases of serotonin syndrome, a potentially life-threatening condition, have been reported during concomitant use of opioids with serotonergic drugs [see Drug Interactions (7)].

Adrenal insufficiency: Cases of adrenal insufficiency have been reported with opioid use, more often following greater than one month of use [see Warnings and Precautions (5.8)].

Anaphylaxis: Anaphylactic reaction has been reported with ingredients contained in Oxycodone Hydrochloride Tablets [see Contraindications (4)].

Androgen deficiency: Cases of androgen deficiency have occurred with chronic use of opioids [see Clinical Pharmacology (12.2)].

7 DRUG INTERACTIONS

Table 1 includes clinically significant drug interactions with Oxycodone Hydrochloride Tablets

Table 1: Clinically Significant Drug Interactions with OXYCODONE HYDROCHLORIDE TABLETS

Inhibitors of CYP3A4 and CYP2D6
Clinical Impact: | The concomitant use of Oxycodone Hydrochloride Tablets, USP and CYP3A4 inhibitors can increase the plasma concentration of oxycodone, resulting in increased or prolonged opioid effects. These effects could be more pronounced with concomitant use of Oxycodone Hydrochloride Tablets, USP and CYP2D6 and CYP3A4 inhibitors, particularly when an inhibitor is added after a stable dose of Oxycodone Hydrochloride Tablets, USP is achieved [see Warnings and Precautions (5.4)]. After stopping a CYP3A4 inhibitor, as the effects of the inhibitor decline, the oxycodone plasma concentration will decrease [see Clinical Pharmacology (12.3)], resulting in decreased opioid efficacy or a withdrawal syndrome in patients who had developed physical dependence to oxycodone.
Intervention: | If concomitant use is necessary, consider dosage reduction of Oxycodone Hydrochloride Tablets, USP until stable drug effects are achieved. Monitor patients for respiratory depression and sedation at frequent intervals. If a CYP3A4 inhibitor is discontinued, consider increasing the Oxycodone Hydrochloride Tablets, USP dosage until stable drug effects are achieved. Monitor for signs of opioid withdrawal.
Examples: | Macrolide antibiotics (e.g., erythromycin), azole-antifungal agents (e.g.,ketoconazole), protease inhibitors (e.g., ritonavir).
CYP3A4 Inducers
Clinical Impact: | The concomitant use of Oxycodone Hydrochloride Tablets, USP and CYP3A4 inducers can decrease the plasma concentration of oxycodone [see Clinical Pharmacology (12.3)], resulting in decreased efficacy or onset of a withdrawal syndrome in patients who have developed physical dependence to oxycodone [see Warnings and Precautions (5.12)]. After stopping a CYP3A4 inducer, as the effects of the inducer decline, the oxycodone plasma concentration will increase [see Clinical Pharmacology (12.3)], which could increase or prolong both the therapeutic effects and adverse reactions, and may cause serious respiratory depression.
Intervention: | If concomitant use is necessary, consider increasing the Oxycodone Hydrochloride Tablets, USP dosage until stable drug effects are achieved. Monitor for signs of opioid withdrawal. If a CYP3A4 inducer is discontinued, consider Oxycodone Hydrochloride Tablets, USP dosage reduction and monitor for signs of respiratory depression.
Examples: | Rifampin, carbamazepine, phenytoin
B enzodi az epin es and O th er C en tr al N er v ous S y s t em (CN S) D e pr es s an ts
Clinical Impact: | Due to additive pharmacologic effect, the concomitant use of benzodiazepines or other CNS depressants, including alcohol, can increase the risk of hypotension, respiratory depression, profound sedation, coma, and death.
Intervention: | Reserve concomitant prescribing of these drugs for use in patients for whom alternative treatment options are inadequate. Limit dosages and durations to the minimum required. Follow patients closely for signs of respiratory depression and sedation [see Warnings and Precautions (5.5)].
Example: | Benzodiazepines and other sedatives/hypnotics, anxiolytics, tranquilizers, muscle relaxants, general anesthetics, antipsychotics, other opioids, alcohol.
Serotonergic Drugs
Clinical Impact: | The concomitant use of opioids with other drugs that affect the serotonergic neurotransmitter system has resulted in serotonin syndrome [see Adverse Reactions (6.2)].
Intervention: | If concomitant use is warranted, carefully observe the patient, particularly during treatment initiation and dose adjustment. Discontinue Oxycodone Hydrochloride Tablets, USP if serotonin syndrome is suspected.
Example: | Selective serotonin reuptake inhibitors (SSRIs), serotonin and norepinephrine reuptake inhibitors (SNRIs), tricyclic antidepressants (TCAs), triptans, 5-HT3 receptor antagonists, drugs that affect the serotonin neurotransmitter system (e.g., mirtazapine, trazodone, tramadol), monoamine oxidase (MAO) inhibitors (those intended to treat psychiatric disorders and also others, such as linezolid and intravenous methylene blue).
Monoamine Oxidase Inhibitors (MAOIs)
Clinical Impact: | MAOI interactions with opioids may manifest as serotonin syndrome or opioid toxicity (e.g., respiratory depression, coma) [see Warnings and Precautions (5.2)].
Intervention: | The use of Oxycodone Hydrochloride Tablets, USP is not recommended for patients taking MAOIs or within 14 days of stopping such treatment. If urgent use of an opioid is necessary, use test doses and frequent titration of small doses to treat pain while closely monitoring blood pressure and signs and symptoms of CNS and respiratory depression.
Examples: | phenelzine, tranylcypromine, linezolid
Mixed Agonist/Antagonist Opioid Analgesics
Clinical Impact: | May reduce the analgesic effect of Oxycodone Hydrochloride Tablets, USP and/or may precipitate withdrawal symptoms.
Intervention: | Avoid concomitant use
Examples: | Butorphanol, nalbuphine, pentazocine, buprenorphine
Muscle Relaxants
Clinical Impact: | Oxycodone may enhance the neuromuscular blocking action of skeletal muscle relaxants and produce an increased degree of respiratory depression.
Intervention: | Monitor patients for signs of respiratory depression that may be greater than otherwise expected and decrease the dosage of Oxycodone Hydrochloride Tablets, USP and/or the muscle relaxant as necessary.
Diuretics
Clinical Impact: | Opioids can reduce the efficacy of diuretics by inducing the release of antidiuretic hormone.
Intervention: | Monitor patients for signs of dismissed diuresis and/or effects on blood pressure and increase the dosage of the diuretic as needed.
Anticholinergic Drugs
Clinical Impact: | The concomitant risk of anticholinergic drugs may result in increased risk of urinary retention and/or severe constipation, which may lead to paralytic ileus.
Intervention: | Monitor patients for signs of urinary retention or reduced gastric motility when Oxycodone Hydrochloride Tablets, USP is used concurrently with anticholinergic drugs.

8 USE IN SPECIFIC POPULATIONS

8.1 Pregnancy

Risk Summary
Prolonged use of opioid analgesics during pregnancy may cause neonatal opioid withdrawal syndrome [see Warnings and Precautions (5.4)]. Available data with Oxycodone Hydrochloride Tablets in pregnant women are insufficient to inform a drug-associated risk for major birth defects and miscarriage. Animal reproduction studies with oral administrations of oxycodone HCl in rats and rabbits during the period of organogenesis at doses 2.6 and 8.1 times, respectively, the human dose of 60 mg/day did not reveal evidence of teratogenicity or embryo-fetal toxicity. In several published studies, treatment of pregnant rats with oxycodone at clinically relevant doses and below, resulted in neurobehavioral effects in offspring [see Data]. Based on animal data, advise pregnant women of the potential risk to a fetus
.

All pregnancies have a background risk of birth defect, loss, or other adverse outcomes. In the U.S. general population, the estimated background risk of major birth defects and miscarriage in clinically recognized pregnancies is 2 to 4% and 15 to 20%, respectively.

Clinical Considerations
Fetal/Neonatal Adverse Reactions
Prolonged use of opioid analgesics during pregnancy for medical or nonmedical purposes can result in physical dependence in the neonate and neonatal opioid withdrawal syndrome shortly after birth.

Neonatal opioid withdrawal syndrome presents irritability, hyperactivity, and abnormal sleep pattern, high pitched cry, tremor, vomiting, diarrhea, and failure to gain weight. The onset, duration, and severity of neonatal opioid withdrawal syndrome vary based on the specific opioid use, duration of use, timing and amount of last maternal use, and rate of elimination of the drug by the newborn. Observe newborns for symptoms of neonatal opioid withdrawal syndrome and manage accordingly [see Warnings and Precautions (5.4)].

Labor or Delivery
Opioids cross the placenta and may produce respiratory depression and psycho-physiologic effects in neonates. An opioid antagonist such as naloxone, must be available for reversal of opioid-induced respiratory depression in the neonate. Oxycodone Hydrochloride Tablets is not recommended for use in pregnant women during or immediately prior to labor, when other analgesic techniques are more appropriate. Opioid analgesics, including Oxycodone Hydrochloride Tablets, can prolong labor through actions which temporarily reduce the strength, duration and frequency of uterine contractions. However, this effect is not consistent and may be offset by an increased rate of cervical dilation, which tends to shorten labor. Monitor neonates exposed to opioid analgesics during labor for signs of excess sedation and respiratory depression.

Data
Animal Data
In embryo-fetal development studies in rats and rabbits, pregnant animals received oral doses of oxycodone HCl administered during the period of organogenesis up to 16 mg/kg/day and up to 25 mg/kg/day, respectively. These studies revealed no evidence of teratogenicity or embryo-fetal toxicity due to oxycodone. The highest doses tested in rats and rabbits were equivalent to approximately 2.6 and 8.1 times an adult human dose of 60 mg/day, respectively, on a mg/m2 basis. In published studies, offspring of pregnant rats administered oxycodone during gestation have been reported to exhibit neurobehavioral effects including altered stress responses, increased anxiety-like behavior (2 mg/kg/day IV from Gestation Day 8 to 21 and Postnatal Day 1, 3, and 5; 0.3 times an adult human dose of 60 mg/day, on a mg/m2 basis) and altered learning and memory (15 mg/kg/day orally from breeding through parturition; 2.4 times an adult human dose of 60 mg/day, on a mg/m^2 basis).

8.2 Labor & Delivery

Risk Summary
Oxycodone is present in breast milk. Published lactation studies report variable concentrations of oxycodone in breast milk with administration of immediate-release oxycodone to nursing mothers in the early postpartum period. The lactation studies did not assess breastfed infants for potential adverse reactions. Lactation studies have not been conducted with Oxycodone Hydrochloride Tablets, and no information is available on the effects of the drug on the breastfed infant or the effects of the drug on milk production.

The developmental and health benefits of breastfeeding should be considered along with the mother’s clinical need for Oxycodone Hydrochloride Tablets and any potential adverse effects on the breastfed infant from Oxycodone Hydrochloride Tablets or from the underlying maternal condition.

Clinical Considerations
Infants exposed to Oxycodone Hydrochloride Tablets through breast milk should be monitored for excess sedation and respiratory depression. Withdrawal symptoms can occur in breastfed infants when maternal administration of an opioid analgesic is stopped or when breast-feeding is stopped.

8.3 Females and Males of Reproductive Potential

Infertility
Chronic use of opioids may cause reduced fertility in females and males of reproductive potential. It is not known whether these effects on fertility are reversible [see Adverse Reactions (6.2), Clinical Pharmacology (12.2)].

8.4 Pediatric Use

The safety and efficacy of Oxycodone Hydrochloride Tablets in pediatric patients have not been evaluated.

8.5 Geriatric Use

Of the total number of subjects in clinical studies of Oxycodone Hydrochloride Tablets , 20.8% (112/538) were 65 and over, while 7.2% (39/538) were 75 and over. No overall differences in safety or effectiveness were observed between these subjects and younger subjects, and other reported clinical experience has not identified differences in responses between the elderly and younger patients, but greater sensitivity of some older individuals cannot be ruled out.

Elderly patients (aged 65 years or older) may have increased sensitivity to oxycodone. In general, use caution when selecting a dosage for an elderly patient, usually starting at the low end of the dosing range, reflecting the greater frequency of decreased hepatic, renal, or cardiac function and of concomitant disease or other drug therapy.

Respiratory depression is the chief risk for elderly patients treated with opioids, and has occurred after large initial doses were administered to patients who were not opioid-tolerant or when opioids were co-administered with other agents that depress respiration. Titrate the dosage of Oxycodone Hydrochloride Tablets slowly in geriatric patients and monitor closely for signs of central nervous system and respiratory depression [see Warnings and Precautions (5.7)].

Oxycodone is known to be substantially excreted by the kidney, and the risk of adverse reactions to this drug may be greater in patients with impaired renal function. Because elderly patients are more likely to have decreased renal function, care should be taken in dose selection, and it may be useful to monitor renal function.

8.6 Hepatic Impairment

Because oxycodone is extensively metabolized in the liver, its clearance may decrease in patients with hepatic impairment. Initiate therapy in these patients with a lower than usual dosage of Oxycodone Hydrochloride Tablets and titrate carefully. Monitor closely for adverse events such as respiratory depression, sedation, and hypotension [see Clinical Pharmacology (12.3)].

8.7 Renal Impairment

Because oxycodone is known to be substantially excreted by the kidney, its clearance may decrease in patients with renal impairment. Initiate therapy with a lower than usual dosage of Oxycodone Hydrochloride Tablets and titrate carefully. Monitor closely for adverse events such as respiratory depression, sedation, and hypotension [see Clinical Pharmacology (12.3)].

9 DRUG ABUSE AND DEPENDENCE

9.1 Controlled Substance

Oxycodone Hydrochloride Tablets contains oxycodone, a Schedule II controlled substance.

9.2 Abuse

Oxycodone Hydrochloride Tablets contains oxycodone, a substance with a high potential for abuse similar to other opioids including fentanyl, hydrocodone hydromorphone, methadone, morphine, oxymorphone, and tapentadol. Oxycodone Hydrochloride Tablets can be abused and is subject to misuse, addiction, and criminal diversion [see Warnings and Precautions (5.1)].

All patients treated with opioids require careful monitoring for signs of abuse and addiction, because use of opioid analgesic products carries the risk of addiction even under appropriate medical use.

Prescription drug abuse is the intentional non-therapeutic use of a prescription drug, even once, for its rewarding psychological or physiological effects.

Drug addiction is a cluster of behavioral, cognitive, and physiological phenomena that develop after repeated substance use and includes: a strong desire to take the drug, difficulties in controlling its use, persisting in its use despite harmful consequences, a higher priority given to drug use than to other activities and obligations, increased tolerance, and sometimes a physical withdrawal.

“Drug-seeking” behavior is very common in persons with substance use disorders. Drug-seeking tactics include emergency calls or visits near the end of office hours, refusal to undergo appropriate examination, testing or referral, repeated “loss” of prescriptions, tampering with prescriptions, and reluctance to provide prior medical records or contact information for other treating healthcare provider(s). “Doctor shopping” (visiting multiple prescribers to obtain additional prescriptions) is common among drug abusers and people suffering from untreated addiction. Preoccupation with achieving adequate pain relief can be appropriate behavior in a patient with poor pain control.

Abuse and addiction are separate and distinct from physical dependence and tolerance. Healthcare providers should be aware that addiction may not be accompanied by concurrent tolerance and symptoms of physical dependence in all addicts. In addition, abuse of opioids can occur in the absence of true addiction.

Oxycodone Hydrochloride Tablets, like other opioids, can be diverted for non-medical use into illicit channels of distribution. Careful record-keeping of prescribing information, including quantity, frequency, and renewal requests, as required by state and federal law, is strongly advised.

Proper assessment of the patient, proper prescribing practices, periodic re-evaluation of therapy, and proper dispensing and storage are appropriate measures that help to limit abuse of opioid drugs.

Risks Specific to Abuse of Oxycodone Hydrochloride Tablets
Oxycodone Hydrochloride Tablets is for oral use only. Abuse of Oxycodone Hydrochloride Tablets poses a risk of overdose and death. The risk is increased with concurrent abuse of Oxycodone Hydrochloride Tablets with alcohol and other central nervous system depressants.

Parenteral drug abuse is commonly associated with transmission of infectious diseases such as hepatitis and HIV.

9.3 Dependence

Both tolerance and physical dependence can develop during chronic opioid therapy. Tolerance is the need for increasing doses of opioids to maintain a defined effect such as analgesia (in the absence of disease progression or other external factors). Tolerance may occur to both the desired and undesired effects of drugs, and may develop at different rates for different effects.

Physical dependence results in withdrawal symptoms after abrupt discontinuation or a significant dosage reduction of a drug. Withdrawal also may be precipitated through the administration of drugs with opioid antagonist activity (e.g., naloxone, nalmefene), mixed agonist/antagonist analgesics (e.g., pentazocine, butorphanol, nalbuphine), or partial agonists (e.g., buprenorphine). Physical dependence may not occur to a clinically significant degree until after several days to weeks of continued opioid usage.

Oxycodone Hydrochloride Tablets should not be abruptly discontinued in a physically-dependent patient [see Dosage and Administration (2.4)]. If Oxycodone Hydrochloride Tablets is abruptly discontinued in a physically-dependent patient, a withdrawal syndrome may occur. Some or all of the following can characterize this syndrome: restlessness, lacrimation, rhinorrhea, yawning, perspiration, chills, myalgia, and mydriasis. Other signs and symptoms also may develop, including irritability, anxiety, backache, joint pain, weakness, abdominal cramps, insomnia, nausea, anorexia, vomiting, diarrhea, or increased blood pressure, respiratory rate, or heart rate.

Infants born to mothers physically dependent on opioids will also be physically dependent and may exhibit respiratory difficulties and withdrawal signs [see Use in Specific Populations (8.1)].

10 OVERDOSAGE

Clinical Presentation
Acute overdose with Oxycodone Hydrochloride Tablets can be manifested by respiratory depression, somnolence progressing to stupor or coma, skeletal muscle flaccidity, cold and clammy skin, constricted pupils, and in some cases, pulmonary edema, bradycardia, hypotension, partial or complete airway obstruction, atypical snoring, and death. Marked mydriasis rather than miosis may be seen with hypoxia in overdose situations [see Clinical Pharmacology (12.2)].

Treatment of Overdose
In case of overdose, priorities are the re-establishment of a patent and protected airway and institution of assisted or controlled ventilation, if needed. Employ other supportive measures (including oxygen and vasopressors) in the management of circulatory shock and pulmonary edema as indicated. Cardiac arrest or arrhythmias will require advanced life-support techniques.

The opioid antagonists, naloxone or nalmefene, are specific antidotes to respiratory depression resulting from opioid overdose. For clinically significant respiratory or circulatory depression secondary to oxycodone overdose, administer an opioid antagonist. Opioid antagonists should not be administered in the absence of clinically significant respiratory or circulatory depression secondary to oxycodone overdose.

Because the duration of opioid reversal is expected to be less than the duration of action of oxycodone in Oxycodone Hydrochloride Tablets, carefully monitor the patient until spontaneous respiration is reliably reestablished. If the response to an opioid antagonist is suboptimal or only brief in nature, administer additional antagonist as directed by the product’s prescribing information.

In an individual physically dependent on opioids, administration of the recommended usual dosage of the antagonist will precipitate an acute withdrawal syndrome. The severity of the withdrawal symptoms experienced will depend on the degree of physical dependence and the dose of the antagonist administered. If a decision is made to treat serious respiratory depression in the physically dependent patient, administration of the antagonist should be initiated with care and by titration with smaller than usual doses of the antagonist.

11 DESCRIPTION

Oxycodone Hydrochloride Tablets contains oxycodone, an opioid agonist.

Each tablet for oral administration contains 5 mg, 15 mg, or 30 mg, of oxycodone hydrochloride USP.

Oxycodone hydrochloride is a white, odorless crystalline powder derived from the opium alkaloid, thebaine. Oxycodone hydrochloride dissolves in water (1 g in 6 to 7 mL) and is considered slightly soluble in alcohol (octanol water partition coefficient is 0.7).

Chemically, oxycodone hydrochloride is 4, 5α-epoxy-14-hydroxy-3-methoxy-17-methylmorphinan-6 one hydrochloride and has the following structural formula:

C18H21NO4•HCl MW = 351.82
The 5 mg Oxycodone Hydrochloride Tablets tablet contains inactive ingredients: microcrystalline cellulose and stearic acid. The 15 mg and 30 mg tablets contain the following inactive ingredients: microcrystalline cellulose; sodium starch glycolate; corn starch; lactose; stearic acid; D&C Yellow No. 10 (15 mg tablet); and FD&C Blue No. 2 (15 mg and 30 mg tablets).

The 5 mg, 15 mg and 30 mg tablets contain the equivalent of 4.5 mg, 13.5 mg and 27.0 mg, respectively, of oxycodone free base.

12 CLINICAL PHARMACOLOGY

12.1 Mechanism of Action

Oxycodone is a full opioid agonist and is relatively selective for the mu-opioid receptor, although it can bind to other opioid receptors at higher doses. The principal therapeutic action of oxycodone is analgesia. Like all full opioid agonists, there is no ceiling effect for analgesia with oxycodone. Clinically, dosage is titrated to provide adequate analgesia and may be limited by adverse reactions, including respiratory and CNS depression.

The precise mechanism of the analgesic action is unknown. However, specific CNS opioid receptors for endogenous compounds with opioid-like activity have been identified throughout the brain and spinal cord and are thought to play a role in the analgesic effects of this drug.

12.2 Pharmacodynamics

Effects on Central Nervous System
Oxycodone produces respiratory depression by direct action on brain stem respiratory centers. The respiratory depression involves a reduction in the responsiveness of the brain stem respiratory centers to both increases in carbon dioxide tension and electrical stimulation.

Oxycodone causes miosis, even in total darkness. Pinpoint pupils are a sign of opioid overdose but are not pathognomonic (e.g., pontine lesions of hemorrhagic or ischemic origins may produce similar findings). Marked mydriasis rather than miosis may be seen due to hypoxia in overdose situations.

Effects on Gastrointestinal Tract And Other Smooth Muscle
Oxycodone causes a reduction in motility associated with an increase in smooth muscle tone in the antrum of the stomach and duodenum. Digestion of food in the small intestine is delayed and propulsive contractions are decreased. Propulsive peristaltic waves in the colon are decreased, while tone may be increased to the point of spasm, resulting in constipation. Other opioid-induced effects may include a reduction in biliary and pancreatic secretions, spasm of sphincter of Oddi, and transient elevations in serum amylase.

Effects on Cardiovascular System
Oxycodone produces peripheral vasodilatation, which may result in orthostatic hypotension or syncope. Manifestations of histamine release and/or peripheral vasodilatation may include pruritus, flushing, red eyes, sweating, and/or orthostatic hypotension.

Effects on the Endocrine System
Opioids inhibit the secretion of adrenocorticotropic hormone (ACTH), cortisol, and luteinizing hormone (LH) in humans [see Adverse Reactions (6.2)]. They also stimulate prolactin, growth hormone (GH) secretion, and pancreatic secretion of insulin and glucagon.

Chronic use of opioids may influence the hypothalamic-pituitary-gonadal axis, leading to androgen deficiency that may manifest as low libido, impotence, erectile dysfunction, amenorrhea, or infertility. The causal role of opioids in the clinical syndrome of hypogonadism is unknown because the various medical, physical, lifestyle, and psychological stressors that may influence gonadal hormone levels have not been adequately controlled for in studies conducted to date [see Adverse Reactions (6.2)].

Effects on the Immune System
Opioids have been shown to have a variety of effects on components of the immune system in in vitro
and animal models. The clinical significance of these findings is unknown. Overall, the effects of opioids appear to be modestly immunosuppressive.

Concentration-Efficacy Relationships
The minimum effective analgesic concentration will vary widely among patients, especially among patients who have been previously treated with potent agonist opioids. The minimum effective analgesic concentration of oxycodone for any individual patient may increase over time due to an increase in pain, the development of a new pain syndrome, and/or the development of analgesic tolerance [see Dosage and Administration (2.1, 2.3)].

Concentration-Adverse Reaction Relationships
There is a relationship between increasing oxycodone plasma concentration and increasing frequency of dose-related opioid adverse reactions such as nausea, vomiting, CNS effects, and respiratory depression. In opioid-tolerant patients, the situation may be altered by the development of tolerance to opioid-related adverse reactions [see Dosage and Administration (2.1, 2.2, 2.3)].

12.3 Pharmacokinetics

The activity of Oxycodone Hydrochloride Tablets (oxycodone hydrochloride) tablets is primarily due to the parent drug oxycodone. Oxycodone Hydrochloride Tablets tablets are designed to provide immediate release of oxycodone.

Table 2: Pharmacokinetic Parameters (Mean±SD)
Dose\Parameters | AUC (ngxhr/mL) | Cmax (ng/mL) | Tmax (hr) | Cmin (ng/mL) | Cavg (ng/mL) | Half-Life (hr)
Single Dose Pharmacokinetics
Oxycodone Hydrochloride Tablets 5 mg tabs x 3 | 133.2±33 | 22.3±8.2 | 1.8±1.z8 | n/a | n/a | 3.73±0.9
Oxycodone Hydrochloride Tablets 15 mg tab | 128.2±35.1 | 22.2±7.6 | 1.4±0.7 | n/a | n/a | 3.55±1.0
Oxycodone Hydrochloride Tablets Liquid Concentrate 15 mg oral solution | 130.6±34.7 | 21.1±6.1 | 1.9±1.5 | n/a | n/a | 3.71±0.8
Oxycodone Hydrochloride Tablets 30 mg tab | 268.2±60.7 | 39.3±14.0 | 2.6±3.0 | n/a | n/a | 3.85±1.3
Food-Effect, Single Dose
Oxycodone Hydrochloride Tablets 10 mg/10 mL oral sol’n (fasted) | 105±6.2 | 19.0±3.7 | 1.25±0.5 | n/a | n/a | 2.9±0.4
Oxycodone Hydrochloride Tablets 10 mg/10 mL oral sol’n (fed) | 133±25.2 | 17.7±3.0 | 2.54±1.2 | n/a | n/a | 3.3±0.5
Multiple-Dose Studies | AUC (72-84)
Oxycodone Hydrochloride Tablets 5 mg tabs q6h x 14 doses | 113.3±24.0 | 15.7±3.2 | 1.3±0.3 | 7.4±1.8 | 9.4±2.0 | n/a
Oxycodone Hydrochloride Tablets 3.33 mg (3.33 mL) oral sol’n. q4h x 21 doses | 99.0±24.8 | 12.9±3.1 | 1.0±0.3 | 7.2±2.3 | 9.7±2.6 | n/a

Absorption
About 60% to 87% of an oral dose of oxycodone reaches the systemic circulation in comparison to a parenteral dose. This high oral bioavailability (compared to other oral opioids) is due to lower presystemic and/or first-pass metabolism of oxycodone. The relative oral bioavailability of Oxycodone Hydrochloride Tablets 15 mg and 30 mg tablets, compared to the 5 mg Oxycodone Hydrochloride

Tablets, is 96% and 101% respectively. Oxycodone Hydrochloride Tablets 15 mg tablets and 30 mg tablets are bioequivalent to the 5 mg Oxycodone Hydrochloride Tablets (see Table 2 for pharmacokinetic parameters). Dose proportionality of oxycodone has been established using the Oxycodone Hydrochloride Tablets 5 mg tablets at doses of 5 mg, 15 mg (three 5 mg tablets) and 30 mg

(six 5 mg tablets) based on extent of absorption (AUC) (see Figure 1). It takes approximately 18 to 24 hours to reach steady-state plasma concentrations of oxycodone with Oxycodone Hydrochloride Tablets

Food Effect
A single-dose food effect study was conducted in normal volunteers using the 5 mg/5 mL solution. The concurrent intake of a high fat meal was shown to enhance the extent (27% increase in AUC), but not the rate of oxycodone absorption from the oral solution (see Table 2). In addition, food caused a delay in Tmax (1.25 to 2.54 hour). Similar effects of food are expected with the 15 mg and 30 mg tablets.

Distribution
Following intravenous administration, the volume of distribution (Vss) for oxycodone was 2.6 L/kg. Plasma protein binding of oxycodone at 37°C and a pH of 7.4 was about 45%. Oxycodone has been found in breast milk [see Special Populations (8.2)].

Elimination
Metabolism
A high portion of oxycodone is N-dealkylated to noroxycodone during first-pass metabolism, and is catalyzed by CYP3A4. Oxymorphone is formed by the O-demethylation of oxycodone. The metabolism of oxycodone to oxymorphone is catalyzed by CYP2D6 [see Drug Interactions (7)]. Free and conjugated noroxycodone, free and conjugated oxycodone, and oxymorphone are excreted in human urine following a single oral dose of oxycodone. The major circulating metabolite is noroxycodone with an AUC ratio of 0.6 relative to that of oxycodone. Oxymorphone is present in the plasma only in low concentrations. The analgesic activity profile of other metabolites is not known at present.

Excretion
Oxycodone and its metabolites are excreted primarily via the kidney. The amounts measured in the urine have been reported as follows: free oxycodone up to 19%; conjugated oxycodone up to 50%; free oxymorphone 0%; conjugated oxymorphone ≤ 14%; both free and conjugated noroxycodone have been found in the urine but not quantified. The total plasma clearance was
0.8 L/min for adults. Apparent elimination half-life of oxycodone following the administration of Oxycodone Hydrochloride Tablets was 3.5 to 4 hours.

Specific Populations
Age: Geriatric Population
Population pharmacokinetic studies conducted with Oxycodone Hydrochloride Tablets, indicated that the plasma concentrations of oxycodone did not appear to be increased in patients over the age of 65.

Hepatic Impairment
In a clinical trial supporting the development of Oxycodone Hydrochloride Tablets, too few patients with decreased hepatic function were evaluated to study these potential differences. However, because oxycodone is extensively metabolized in the liver, its clearance may decrease in hepatic impaired patients [see Use in Specific Populations (8.6)].

Renal Impairment
This drug is known to be substantially excreted by the kidney, and the risk of adverse reactions to this drug may be greater in patients with impaired renal function [see Use in Specific Populations (8.7)].

13 NONCLINICAL TOXICOLOGY

13.1 Carcinogenesis & Mutagenesis & Impairment Of Fertility

Carcinogenesis
Long-term studies have not been performed in animals to evaluate the carcinogenic potential of Oxycodone Hydrochloride Tablets or oxycodone.

Mutagenesis
Oxycodone hydrochloride was genotoxic in an in vitro mouse lymphoma assay in the presence of metabolic activation. There was no evidence of genotoxic potential in an in vitro bacterial reverse mutation assay (Salmonella typhimurium and Escherichia coli) or in an assay for chromosomal aberrations (in vivo mouse bone marrow micronucleus assay).

Impairment of Fertility
Studies in animals to evaluate the potential impact of oxycodone on fertility have not been conducted.

16 HOW SUPPLIED/STORAGE AND HANDLING

Oxycodone hydrochloride tablets, USP are available as follows:

5 mg
White to off white, round tablets, debossed with U22 on one side and breakline on the other side.

NDC 68071-2368-6 BOTTLES OF 6

DEA Order Form Required

Dispense in a tight, light-resistant container. Protect from moisture.

Store at 20° to 25°C (68° to 77°F). [See USP Controlled Room Temperature.]

DEA Order Form Required.

17 PATIENT COUNSELING INFORMATION

Advise the patient to read the FDA-approved patient labeling (Medication Guide).
Addiction, Abuse and Misuse
Inform patients that the use of Oxycodone Hydrochloride Tablets, even when taken as recommended, can result in addiction, abuse, and misuse, which can lead to overdose and death [see Warnings and Precautions (5.1)]. Instruct patients not to share Oxycodone Hydrochloride Tablets with others and to take steps to protect Oxycodone Hydrochloride Tablets from theft and misuse.
Life-Threatening Respiratory Depression
Inform patients of the risk of life-threatening respiratory depression, including information that the risk is greatest when starting Oxycodone Hydrochloride Tablets or when the dosage is increased, and that it can occur even at recommended dosages [see Warnings and Precautions (5.3)]. Advise patients how to recognize respiratory depression and to seek medical attention if breathing difficulties develop.
Accidental Ingestion
Inform patients that accidental ingestion, especially by children, may result in respiratory depression or death [see Warnings and Precautions (5.3)]. Instruct patients to take steps to store Oxycodone Hydrochloride Tablets securely and to dispose of unused Oxycodone Hydrochloride Tablets by flushing the tablets down the toilet or disposing of in accordance with local state guidelines and/or regulations.
Interactions with Benzodiazepines and Other CNS Depressants
Inform patients and caregivers that potentially fatal additive effects may occur if Oxycodone Hydrochloride Tablets is used with benzodiazepines or other CNS depressants, including alcohol, and not to use these concomitantly unless supervised by a healthcare provider [see Warnings and Precautions (5.6), Drug Interactions (7)].
Serotonin Syndrome
Inform patients that opioids could cause a rare but potentially life-threatening condition resulting from concomitant administration of serotonergic drugs. Warn patients of the symptoms of serotonin syndrome and to seek medical attention right away if symptoms develop. Instruct patients to inform their healthcare providers if they are taking, or plan to take serotonergic medication [see Drug Interactions (7)].
MAOI Interaction
Inform patients to avoid taking Oxycodone Hydrochloride Tablets while using any drugs that inhibit monoamine oxidase. Patients should not start MAOIs while taking Oxycodone Hydrochloride Tablets [see Drug Interactions (7)].
Adrenal Insufficiency
Inform patients that opioids could cause adrenal insufficiency, a potentially life-threatening condition. Adrenal insufficiency may present with non-specific symptoms and signs such as nausea, vomiting, anorexia, fatigue, weakness, dizziness and low blood pressure. Advise patients to seek medical attention if they experience a constellation of these symptoms [see Warnings and Precautions (5.8)].
Important Administration Instructions
Instruct patients how to properly take Oxycodone Hydrochloride Tablets. Patients should be advised not to adjust the dose of Oxycodone Hydrochloride Tablets without consulting the prescribing healthcare provider [see Dosage and Administration (2), Warnings and Precautions (5.13)].

Hypotension
Inform patients that Oxycodone Hydrochloride Tablets may cause orthostatic hypotension and syncope. Instruct patients how to recognize symptoms of low blood pressure and how to reduce the risk of serious consequences should hypotension occur (e.g., sit or lie down, carefully rise from sitting or lying position) [see Warnings and Precautions (5.9)].
Anaphylaxis
Inform patients that anaphylaxis has been reported with ingredients contained in Oxycodone Hydrochloride Tablets. Advise patients how to recognize such a reaction and when to seek medical attention [see Contraindications (4), Adverse Reactions (6.2)].
Pregnancy
Neonatal Opioid Withdrawal Syndrome
Inform female patients of reproductive potential that prolonged use of Oxycodone Hydrochloride Tablets during pregnancy can result in neonatal opioid withdrawal syndrome, which may be life-threatening if not recognized and treated [see Warnings and Precautions (5.4), Use in Specific Populations (8.1)].
Embryo-Fetal Toxicity
Inform female patients of reproductive potential that Oxycodone Hydrochloride Tablets can cause fetal harm and to inform their healthcare provider of a known or suspected pregnancy [see Use in Specific Populations (8.1)].
Lactation
Advise nursing mothers to monitor infants for increased sleepiness (more than usual), breathing difficulties, or limpness. Instruct nursing mothers to seek immediate medical care if they notice these signs [see Use in Specific Populations (8.2)].
Infertility
Inform patients that chronic use of opioids may cause reduced fertility. It is not known whether these effects on fertility are reversible [see Use in Specific Populations (8.3)].
Driving or Operating Machinery
Inform patients that Oxycodone Hydrochloride Tablets may impair the ability to perform potentially hazardous activities such as driving a car or operating dangerous machinery. Advise patients not to perform such tasks until they know how they will react to the medication [see Warnings and Precautions (5.14)].
Constipation
Advise patients of the potential for severe constipation, including management instructions and when to seek medical attention [see Adverse Reactions (6), Clinical Pharmacology (12.1)].
Disposal of Unused Oxycodone Hydrochloride Tablets
Advise patients to dispose of unused Oxycodone Hydrochloride Tablets by flushing the tablets down the toilet or disposing of in accordance with local state guidelines and/or regulations.

This Medication Guide has been approved by the U.S. Food and Drug Administration.

Dispense with Medication Guide available at www.aurobindousa.com/product-medication-guides

Distributed by:
Aurobindo Pharma USA, Inc.
279 Princeton-Hightstown Road
East Windsor, NJ 08520 Oxycodone Hydrochloride Tablets

Revised: 12/2018